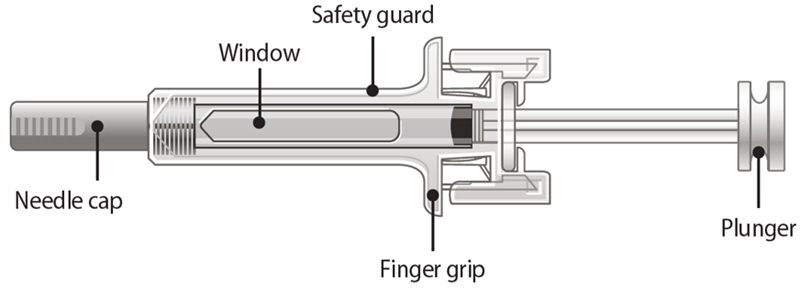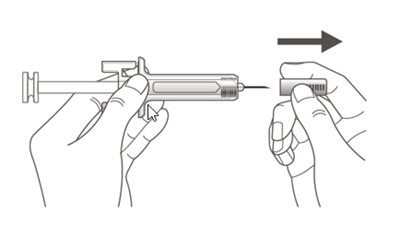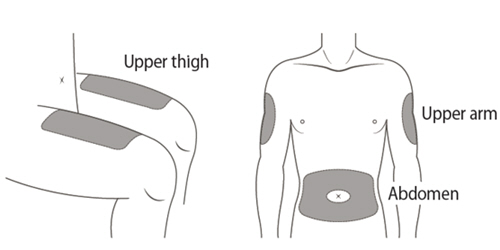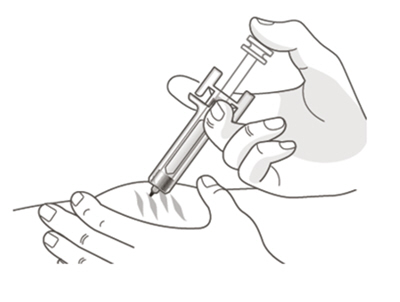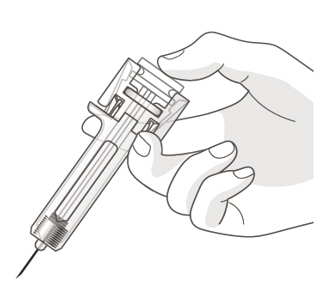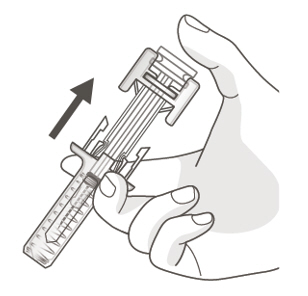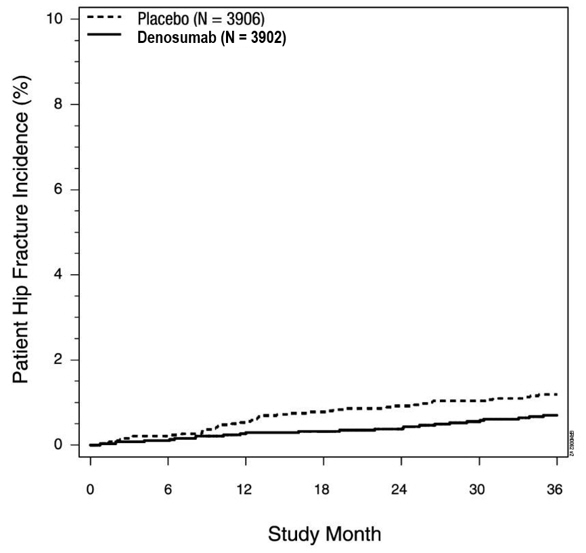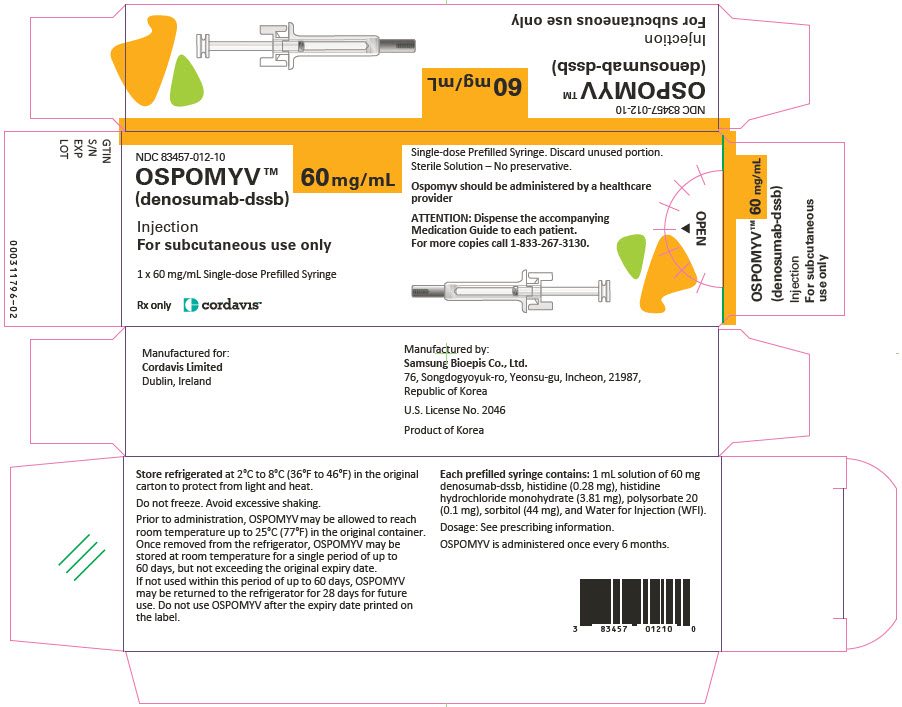 DRUG LABEL: OSPOMYV
NDC: 83457-012 | Form: INJECTION, SOLUTION
Manufacturer: Cordavis Limited
Category: prescription | Type: HUMAN PRESCRIPTION DRUG LABEL
Date: 20251111

ACTIVE INGREDIENTS: DENOSUMAB 60 mg/1 mL
INACTIVE INGREDIENTS: HISTIDINE; HISTIDINE HYDROCHLORIDE MONOHYDRATE; POLYSORBATE 20; SORBITOL; WATER

HIGHLIGHTS OF PRESCRIBING INFORMATION

These highlights do not include all the information needed to use OSPOMYV safely and effectively. See full prescribing information for OSPOMYV.
OSPOMYV™ (denosumab-dssb) injection, for subcutaneous use
Initial U.S. Approval: 2025
OSPOMYV (denosumab-dssb) is biosimilar [Biosimilar means that the biological product is approved based on data demonstrating that it is highly similar to an FDA-approved biological product, known as a reference product, and that there are no clinically meaningful differences between the biosimilar product and the reference product. Biosimilarity of OSPOMYV has been demonstrated for the condition(s) of use (e.g., indication(s), dosing regimen(s)), strength(s), dosage form(s), and route(s) of administration described in its Full Prescribing Information.] to PROLIA (denosumab).

WARNING: SEVERE HYPOCALCEMIA IN PATIENTS WITH ADVANCED KIDNEY DISEASE

See full prescribing information for complete boxed warning.

- Patients with advanced chronic kidney disease are at greater risk of severe hypocalcemia following denosumab products administration. Severe hypocalcemia resulting in hospitalization, life-threatening events and fatal cases have been reported. (5.1)
- The presence of chronic kidney disease-mineral bone disorder (CKD-MBD) markedly increases the risk of hypocalcemia. (5.1)
- Prior to initiating Ospomyv in patients with advanced chronic kidney disease, evaluate for the presence of CKD-MBD. Treatment with Ospomyv in these patients should be supervised by a healthcare provider with expertise in the diagnosis and management of CKD-MBD. (2.2), (5.1)

1 INDICATIONS AND USAGE

Ospomyv is a RANK ligand (RANKL) inhibitor indicated for treatment:

- of postmenopausal women with osteoporosis at high risk for fracture (1.1)
- to increase bone mass in men with osteoporosis at high risk for fracture (1.2)
- of glucocorticoid-induced osteoporosis in men and women at high risk for fracture (1.3)
- to increase bone mass in men at high risk for fracture receiving androgen deprivation therapy for nonmetastatic prostate cancer (1.4)
- to increase bone mass in women at high risk for fracture receiving adjuvant aromatase inhibitor therapy for breast cancer (1.5)

2 DOSAGE AND ADMINISTRATION

- Pregnancy must be ruled out prior to administration of Ospomyv. (2.1)
- Before initiating Ospomyv in patients with advanced chronic kidney disease, including dialysis patients, evaluate for the presence of chronic kidney disease mineral and bone disorder with intact parathyroid hormone, serum calcium, 25(OH) vitamin D, and 1,25(OH)2 vitamin D. (2.2, 5.1, 8.6)
- Ospomyv should be administered by a healthcare provider. (2.3)
- Administer 60 mg every 6 months as a subcutaneous injection in the upper arm, upper thigh, or abdomen. (2.3)
- Instruct patients to take calcium 1000 mg daily and at least 400 IU vitamin D daily. (2.3)

3 DOSAGE FORMS AND STRENGTHS

- Injection: 60 mg/mL solution in single-dose prefilled syringe (3)

4 CONTRAINDICATIONS

- Hypocalcemia (4, 5.1)
- Pregnancy (4, 8.1)
- Known hypersensitivity to denosumab products (4, 5.3)

5 WARNINGS AND PRECAUTIONS

- Hypocalcemia: Pre-existing hypocalcemia must be corrected before initiating Ospomyv. May worsen, especially in patients with renal impairment. Adequately supplement all patients with calcium and vitamin D.
  Concomitant use of calcimimetic drugs may also worsen hypocalcemia risk. Evaluate for presence of chronic kidney disease mineral-bone disorder. Monitor serum calcium. (5.1)
- Same Active Ingredient: Patients receiving Ospomyv should not receive other denosumab products concomitantly. (5.2)
- Hypersensitivity including anaphylactic reactions may occur.
  Discontinue permanently if a clinically significant reaction occurs. (5.3)
- Osteonecrosis of the jaw: Has been reported with denosumab products. Monitor for symptoms. (5.4)
- Atypical femoral fractures: Have been reported. Evaluate patients with thigh or groin pain to rule out a femoral fracture. (5.5)
- Multiple vertebral fractures have been reported following treatment discontinuation. Patients should be transitioned to another antiresorptive agent if Ospomyv is discontinued. (5.6)
- Serious infections including skin infections: May occur, including those leading to hospitalization. Advise patients to seek prompt medical attention if they develop signs or symptoms of infection, including cellulitis. (5.7)
- Dermatologic reactions: Dermatitis, rashes, and eczema have been reported. Consider discontinuing Ospomyv if severe symptoms develop. (5.8)
- Severe bone, joint, muscle pain may occur. Discontinue use if severe symptoms develop. (5.9)
- Suppression of bone turnover: Significant suppression has been demonstrated. Monitor for consequences of bone over-suppression. (5.10)

6 ADVERSE REACTIONS

- Postmenopausal osteoporosis: Most common adverse reactions (> 5% and more common than placebo) were: back pain, pain in extremity, hypercholesterolemia, musculoskeletal pain, and cystitis. Pancreatitis has been reported in clinical trials. (6.1)
- Male osteoporosis: Most common adverse reactions (> 5% and more common than placebo) were: back pain, arthralgia, and nasopharyngitis. (6.1)
- Glucocorticoid-induced osteoporosis: Most common adverse reactions (> 3% and more common than active-control group) were: back pain, hypertension, bronchitis, and headache. (6.1)
- Bone loss due to hormone ablation for cancer: Most common adverse reactions (≥ 10% and more common than placebo) were: arthralgia and back pain. Pain in extremity and musculoskeletal pain have also been reported in clinical trials. (6.1)

To report SUSPECTED ADVERSE REACTIONS, contact Cordavis at 1-833-267-3130 or FDA at 1-800-FDA-1088 or www.fda.gov/medwatch.

8 USE IN SPECIFIC POPULATIONS

- Pregnant women and females of reproductive potential: Denosumab products may cause fetal harm when administered to pregnant women. Advise females of reproductive potential to use effective contraception during therapy, and for at least 5 months after the last dose of Ospomyv. (8.1, 8.3)
- Pediatric patients: Ospomyv is not approved for use in pediatric patients. (8.4)
- Renal impairment: No dose adjustment is necessary in patients with renal impairment. Patients with advanced chronic kidney disease (eGFR <30 mL/min/1.73 m^2), including dialysis-dependent patients, are at greater risk of severe hypocalcemia. The presence of underlying chronic kidney disease-mineral bone disorder markedly increases the risk of hypocalcemia. (5.1, 8.6)

FULL PRESCRIBING INFORMATION

WARNING: SEVERE HYPOCALCEMIA IN PATIENTS WITH ADVANCED KIDNEY DISEASE

- Patients with advanced chronic kidney disease (eGFR <30 mL/min/1.73 m^2), including dialysis-dependent patients, are at greater risk of severe hypocalcemia following denosumab products administration. Severe hypocalcemia resulting in hospitalization, life-threatening events and fatal cases have been reported [see Warnings and Precautions (5.1)].
- The presence of chronic kidney disease-mineral bone disorder (CKD-MBD) markedly increases the risk of hypocalcemia in these patients [see Warnings and Precautions (5.1)].
- Prior to initiating Ospomyv in patients with advanced chronic kidney disease, evaluate for the presence of CKD-MBD. Treatment with Ospomyv in these patients should be supervised by a healthcare provider with expertise in the diagnosis and management of CKD-MBD [see Dosage and Administration (2.2) and Warnings and Precautions (5.1)].

1 INDICATIONS AND USAGE

1.1 Treatment of Postmenopausal Women with Osteoporosis at High Risk for Fracture

Ospomyv is indicated for the treatment of postmenopausal women with osteoporosis at high risk for fracture, defined as a history of osteoporotic fracture, or multiple risk factors for fracture; or patients who have failed or are intolerant to other available osteoporosis therapy. In postmenopausal women with osteoporosis, denosumab reduces the incidence of vertebral, nonvertebral, and hip fractures [see Clinical Studies (14.1)].

1.2 Treatment to Increase Bone Mass in Men with Osteoporosis

Ospomyv is indicated for treatment to increase bone mass in men with osteoporosis at high risk for fracture, defined as a history of osteoporotic fracture, or multiple risk factors for fracture; or patients who have failed or are intolerant to other available osteoporosis therapy [see Clinical Studies (14.2)].

1.3 Treatment of Glucocorticoid-Induced Osteoporosis

Ospomyv is indicated for the treatment of glucocorticoid-induced osteoporosis in men and women at high risk of fracture who are either initiating or continuing systemic glucocorticoids in a daily dosage equivalent to 7.5 mg or greater of prednisone and expected to remain on glucocorticoids for at least 6 months. High risk of fracture is defined as a history of osteoporotic fracture, multiple risk factors for fracture, or patients who have failed or are intolerant to other available osteoporosis therapy [see Clinical Studies (14.3)].

1.4 Treatment of Bone Loss in Men Receiving Androgen Deprivation Therapy for Prostate Cancer

Ospomyv is indicated as a treatment to increase bone mass in men at high risk for fracture receiving androgen deprivation therapy (ADT) for nonmetastatic prostate cancer. In these patients denosumab also reduced the incidence of vertebral fractures [see Clinical Studies (14.4)].

1.5 Treatment of Bone Loss in Women Receiving Adjuvant Aromatase Inhibitor Therapy for Breast Cancer

Ospomyv is indicated as a treatment to increase bone mass in women at high risk for fracture receiving adjuvant aromatase inhibitor therapy for breast cancer [see Clinical Studies (14.5)].

2 DOSAGE AND ADMINISTRATION

2.1 Pregnancy Testing Prior to Initiation of Ospomyv

Pregnancy must be ruled out prior to administration of Ospomyv. Perform pregnancy testing in all females of reproductive potential prior to administration of Ospomyv. Based on findings in animals, denosumab products can cause fetal harm when administered to pregnant women [see Use in Specific Populations (8.1, 8.3)].

2.2 Laboratory Testing in Patients with Advanced Chronic Kidney Disease Prior to Initiation of Ospomyv

In patients with advanced chronic kidney disease [i.e., estimated glomerular filtration rate (eGFR) <30 mL/min/1.73 m^2], including dialysis-dependent patients, evaluate for the presence of chronic kidney disease mineral and bone disorder (CKD-MBD) with intact parathyroid hormone (iPTH), serum calcium, 25(OH) vitamin D, and 1,25 (OH)2 vitamin D prior to decisions regarding Ospomyv treatment. Consider also assessing bone turnover status (serum markers of bone turnover or bone biopsy) to evaluate the underlying bone disease that may be present [see Warnings and Precautions (5.1)].

2.3 Recommended Dosage

Ospomyv should be administered by a healthcare provider.

The recommended dose of Ospomyv is 60 mg administered as a single subcutaneous injection once every 6 months. Administer Ospomyv via subcutaneous injection in the upper arm, the upper thigh, or the abdomen. All patients should receive calcium 1000 mg daily and at least 400 IU vitamin D daily [see Warnings and Precautions (5.1)].

If a dose of Ospomyv is missed, administer the injection as soon as the patient is available. Thereafter, schedule injections every 6 months from the date of the last injection.

2.4 Preparation and Administration

Parenteral drug products should be inspected visually for particulate matter and discoloration prior to administration whenever solution and container permit. Ospomyv is a clear, colorless to slightly yellow solution. Do not use if the solution is discolored or cloudy or if the solution contains particles or foreign particulate matter.

Prior to administration, Ospomyv may be removed from the refrigerator and brought to room temperature up to 25°C (77°F) by standing in the original container. This generally takes 15 to 30 minutes. Do not warm Ospomyv in any other way [see How Supplied/Storage and Handling (16)].

Instructions for Administration of Ospomyv Prefilled Syringe with Needle Safety Guard

IMPORTANT: In order to minimize accidental needlesticks, the Ospomyv single-dose prefilled syringe will have a safety guard that is automatically activated to cover the needle after the injection is given.

Step 1: Remove needle cap

Remove needle cap.

Step 2: Administer subcutaneous injection

Choose an injection site. The recommended injection sites for Ospomyv include: the upper arm OR the upper thigh OR the abdomen.

Insert needle and inject all the liquid subcutaneously.
Do not administer into muscle or blood vessel.

DO NOT put needle cap back on needle.

Step 3: Release the plunger to activate the safety guard
Slowly take your thumb off the plunger head.
After releasing the plunger, the safety guard will safely cover the injection needle.

Immediately dispose of the syringe and needle cap in the nearest sharps container. DO NOT put the needle cap back on the used syringe.

3 DOSAGE FORMS AND STRENGTHS

- Injection: 60 mg/mL clear, colorless to slightly yellow solution in a single-dose prefilled syringe.

4 CONTRAINDICATIONS

Ospomyv is contraindicated in:

- Patients with hypocalcemia: Pre-existing hypocalcemia must be corrected prior to initiating therapy with Ospomyv [see Warnings and Precautions (5.1)].
- Pregnant women: Denosumab products may cause fetal harm when administered to a pregnant woman. In women of reproductive potential, pregnancy testing should be performed prior to initiating treatment with Ospomyv [see Use in Specific Populations (8.1)].
- Patients with hypersensitivity to denosumab products: Ospomyv is contraindicated in patients with a history of systemic hypersensitivity to any component of the product. Reactions have included anaphylaxis, facial swelling, and urticaria [see Warnings and Precautions (5.3), Adverse Reactions (6.2)].

5 WARNINGS AND PRECAUTIONS

5.1 Severe Hypocalcemia and Mineral Metabolism Changes

Denosumab products can cause severe hypocalcemia and fatal cases have been reported. Pre-existing hypocalcemia must be corrected prior to initiating therapy with Ospomyv. Adequately supplement all patients with calcium and vitamin D [see Dosage and Administration (2.1), Contraindications (4), and Adverse Reactions (6.1)].

In patients without advanced chronic kidney disease who are predisposed to hypocalcemia and disturbances of mineral metabolism (e.g. history of hypoparathyroidism, thyroid surgery, parathyroid surgery, malabsorption syndromes, excision of small intestine, treatment with other calcium-lowering drugs), assess serum calcium and mineral levels (phosphorus and magnesium) 10 to 14 days after Ospomyv injection. In some postmarketing cases, hypocalcemia persisted for weeks or months and required frequent monitoring and intravenous and/or oral calcium replacement, with or without vitamin D.

Patients with Advanced Chronic Kidney Disease

Patients with advanced chronic kidney disease [i.e., eGFR <30 mL/min/1.73 m^2] including dialysis-dependent patients are at greater risk for severe hypocalcemia following denosumab products administration. Severe hypocalcemia resulting in hospitalization, life-threatening events and fatal cases have been reported. The presence of underlying chronic kidney disease-mineral bone disorder (CKD-MBD, renal osteodystrophy) markedly increases the risk of hypocalcemia. Concomitant use of calcimimetic drugs may also worsen hypocalcemia risk.

To minimize the risk of hypocalcemia in patients with advanced chronic kidney disease, evaluate for the presence of chronic kidney disease mineral and bone disorder with intact parathyroid hormone (iPTH), serum calcium, 25(OH) vitamin D, and 1,25(OH)2 vitamin D prior to decisions regarding Ospomyv treatment. Consider also assessing bone turnover status (serum markers of bone turnover or bone biopsy) to evaluate the underlying bone disease that may be present. Monitor serum calcium weekly for the first month after Ospomyv administration and monthly thereafter. Instruct all patients with advanced chronic kidney disease, including those who are dialysis-dependent, about the symptoms of hypocalcemia and the importance of maintaining serum calcium levels with adequate calcium and activated vitamin D supplementation. Treatment with Ospomyv in these patients should be supervised by a healthcare provider who is experienced in diagnosis and management of CKD-MBD.

5.2 Drug Products with Same Active Ingredient

Patients receiving Ospomyv should not receive other denosumab products concomitantly.

5.3 Hypersensitivity

Clinically significant hypersensitivity including anaphylaxis has been reported with denosumab products. Symptoms have included hypotension, dyspnea, throat tightness, facial and upper airway edema, pruritus, and urticaria. If an anaphylactic or other clinically significant allergic reaction occurs, initiate appropriate therapy and discontinue further use of Ospomyv [see Contraindications (4), Adverse Reactions (6.2)].

5.4 Osteonecrosis of the Jaw

Osteonecrosis of the jaw (ONJ), which can occur spontaneously, is generally associated with tooth extraction and/or local infection with delayed healing. ONJ has been reported in patients receiving denosumab products [see Adverse Reactions (6.1)]. A routine oral exam should be performed by the prescriber prior to initiation of Ospomyv treatment. A dental examination with appropriate preventive dentistry is recommended prior to treatment with Ospomyv in patients with risk factors for ONJ such as invasive dental procedures (e.g. tooth extraction, dental implants, oral surgery), diagnosis of cancer, concomitant therapies (e.g. chemotherapy, corticosteroids, angiogenesis inhibitors), poor oral hygiene, and comorbid disorders (e.g. periodontal and/or other pre-existing dental disease, anemia, coagulopathy, infection, ill-fitting dentures). Good oral hygiene practices should be maintained during treatment with Ospomyv. Concomitant administration of drugs associated with ONJ may increase the risk of developing ONJ. The risk of ONJ may increase with duration of exposure to denosumab products.

For patients requiring invasive dental procedures, clinical judgment of the treating physician and/or oral surgeon should guide the management plan of each patient based on individual benefit-risk assessment.

Patients who are suspected of having or who develop ONJ while on Ospomyv should receive care by a dentist or an oral surgeon. In these patients, extensive dental surgery to treat ONJ may exacerbate the condition. Discontinuation of Ospomyv therapy should be considered based on individual benefit-risk assessment.

5.5 Atypical Subtrochanteric and Diaphyseal Femoral Fractures

Atypical low energy or low trauma fractures of the shaft have been reported in patients receiving denosumab products [see Adverse Reactions (6.1)]. These fractures can occur anywhere in the femoral shaft from just below the lesser trochanter to above the supracondylar flare and are transverse or short oblique in orientation without evidence of comminution. Causality has not been established as these fractures also occur in osteoporotic patients who have not been treated with antiresorptive agents.

Atypical femoral fractures most commonly occur with minimal or no trauma to the affected area. They may be bilateral, and many patients report prodromal pain in the affected area, usually presenting as dull, aching thigh pain, weeks to months before a complete fracture occurs. A number of reports note that patients were also receiving treatment with glucocorticoids (e.g. prednisone) at the time of fracture.

During Ospomyv treatment, patients should be advised to report new or unusual thigh, hip, or groin pain. Any patient who presents with thigh or groin pain should be suspected of having an atypical fracture and should be evaluated to rule out an incomplete femur fracture. Patients presenting with an atypical femur fracture should also be assessed for symptoms and signs of fracture in the contralateral limb. Interruption of Ospomyv therapy should be considered, pending a benefit-risk assessment, on an individual basis.

5.6 Multiple Vertebral Fractures (MVF) Following Discontinuation of Treatment

Following discontinuation of denosumab treatment, fracture risk increases, including the risk of multiple vertebral fractures. Treatment with denosumab results in significant suppression of bone turnover and cessation of denosumab treatment results in increased bone turnover above pretreatment values 9 months after the last dose of denosumab. Bone turnover then returns to pretreatment values 24 months after the last dose of denosumab. In addition, bone mineral density (BMD) returns to pretreatment values within 18 months after the last injection [see Clinical Pharmacology (12.2), Clinical Studies (14.1)].

New vertebral fractures occurred as early as 7 months (on average 19 months) after the last dose of denosumab. Prior vertebral fracture was a predictor of multiple vertebral fractures after denosumab discontinuation.
Evaluate an individual's benefit-risk before initiating treatment with Ospomyv.

If Ospomyv treatment is discontinued, patients should be transitioned to an alternative antiresorptive therapy [see Adverse Reactions (6.1)].

5.7 Serious Infections

In a clinical trial of over 7800 women with postmenopausal osteoporosis, serious infections leading to hospitalization were reported more frequently in the denosumab group than in the placebo group [see Adverse Reactions (6.1)]. Serious skin infections, as well as infections of the abdomen, urinary tract, and ear, were more frequent in patients treated with denosumab. Endocarditis was also reported more frequently in denosumab-treated patients. The incidence of opportunistic infections was similar between placebo and denosumab groups, and the overall incidence of infections was similar between the treatment groups. Advise patients to seek prompt medical attention if they develop signs or symptoms of severe infection, including cellulitis.

Patients on concomitant immunosuppressant agents or with impaired immune systems may be at increased risk for serious infections. Consider the benefit-risk profile in such patients before treating with Ospomyv. In patients who develop serious infections while on Ospomyv, prescribers should assess the need for continued Ospomyv therapy.

5.8 Dermatologic Adverse Reactions

In a large clinical trial of over 7800 women with postmenopausal osteoporosis, epidermal and dermal adverse events such as dermatitis, eczema, and rashes occurred at a significantly higher rate in the denosumab group compared to the placebo group. Most of these events were not specific to the injection site [see Adverse Reactions (6.1)]. Consider discontinuing Ospomyv if severe symptoms develop.

5.9 Musculoskeletal Pain

In postmarketing experience, severe and occasionally incapacitating bone, joint, and/or muscle pain has been reported in patients taking denosumab products [see Adverse Reactions (6.2)]. The time to onset of symptoms varied from one day to several months after starting denosumab products. Consider discontinuing use if severe symptoms develop [see Patient Counseling Information (17)].

5.10 Suppression of Bone Turnover

In clinical trials in women with postmenopausal osteoporosis, treatment with denosumab resulted in significant suppression of bone remodeling as evidenced by markers of bone turnover and bone histomorphometry [see Clinical Pharmacology (12.2), Clinical Studies (14.1)]. The significance of these findings and the effect of long-term treatment with denosumab products are unknown. The long-term consequences of the degree of suppression of bone remodeling observed with denosumab may contribute to adverse outcomes such as osteonecrosis of the jaw, atypical fractures, and delayed fracture healing. Monitor patients for these consequences.

5.11 Hypercalcemia in Pediatric Patients with Osteogenesis Imperfecta

Ospomyv is not approved for use in pediatric patients. Hypercalcemia has been reported in pediatric patients with osteogenesis imperfecta treated with denosumab products. Some cases required hospitalization [see Use in Specific Populations (8.4)].

6 ADVERSE REACTIONS

The following serious adverse reactions are discussed below and also elsewhere in the labeling:

- Severe Hypocalcemia and Mineral Metabolism Changes [see Warnings and Precautions (5.1)]
- Hypersensitivity [see Warnings and Precautions (5.3)]
- Osteonecrosis of the Jaw [see Warnings and Precautions (5.4)]
- Atypical Subtrochanteric and Diaphyseal Femoral Fractures [see Warnings and Precautions (5.5)]
- Multiple Vertebral Fractures (MVF) Following Treatment Discontinuation [see Warnings and Precautions (5.6)]
- Serious Infections [see Warnings and Precautions (5.7)]
- Dermatologic Adverse Reactions [see Warnings and Precautions (5.8)]

The most common adverse reactions reported with denosumab products in patients with postmenopausal osteoporosis are back pain, pain in extremity, musculoskeletal pain, hypercholesterolemia, and cystitis.

The most common adverse reactions reported with denosumab products in men with osteoporosis are back pain, arthralgia, and nasopharyngitis.

The most common adverse reactions reported with denosumab products in patients with glucocorticoid-induced osteoporosis are back pain, hypertension, bronchitis, and headache.

The most common (per patient incidence ≥ 10%) adverse reactions reported with denosumab products in patients with bone loss receiving androgen deprivation therapy for prostate cancer or adjuvant aromatase inhibitor therapy for breast cancer are arthralgia and back pain. Pain in extremity and musculoskeletal pain have also been reported in clinical trials.

The most common adverse reactions leading to discontinuation of denosumab products in patients with postmenopausal osteoporosis are back pain and constipation.

6.1 Clinical Trials Experience

Because clinical studies are conducted under widely varying conditions, adverse reaction rates observed in the clinical studies of a drug cannot be directly compared to rates in the clinical studies of another drug and may not reflect the rates observed in clinical practice.

Treatment of Postmenopausal Women with Osteoporosis

The safety of denosumab in the treatment of postmenopausal osteoporosis was assessed in a 3-year, randomized, double-blind, placebo-controlled, multinational study of 7808 postmenopausal women aged 60 to 91 years. A total of 3876 women were exposed to placebo and 3886 women were exposed to denosumab administered subcutaneously once every 6 months as a single 60 mg dose. All women were instructed to take at least 1000 mg of calcium and 400 IU of vitamin D supplementation per day.

The incidence of all-cause mortality was 2.3% (n = 90) in the placebo group and 1.8% (n = 70) in the denosumab group. The incidence of nonfatal serious adverse events was 24.2% in the placebo group and 25.0% in the denosumab group. The percentage of patients who withdrew from the study due to adverse events was 2.1% and 2.4% for the placebo and denosumab groups, respectively. The most common adverse reactions reported with denosumab in patients with postmenopausal osteoporosis are back pain, pain in extremity, musculoskeletal pain, hypercholesterolemia, and cystitis.

Adverse reactions reported in ≥ 2% of postmenopausal women with osteoporosis and more frequently in the denosumab-treated women than in the placebo-treated women are shown in the table below.

Table 1. Adverse Reactions Occurring in ≥ 2% of Patients with Osteoporosis and More Frequently than in Placebo-treated Patients
Preferred Term | Denosumab (N = 3886) n (%) | Placebo (N = 3876) n (%)
Back pain | 1347 (34.7) | 1340 (34.6)
Pain in extremity | 453 (11.7) | 430 (11.1)
Musculoskeletal pain | 297 (7.6) | 291 (7.5)
Hypercholesterolemia | 280 (7.2) | 236 (6.1)
Cystitis | 228 (5.9) | 225 (5.8)
Vertigo | 195 (5.0) | 187 (4.8)
Upper respiratory tract infection | 190 (4.9) | 167 (4.3)
Edema peripheral | 189 (4.9) | 155 (4.0)
Sciatica | 178 (4.6) | 149 (3.8)
Bone pain | 142 (3.7) | 117 (3.0)
Abdominal pain upper | 129 (3.3) | 111 (2.9)
Anemia | 129 (3.3) | 107 (2.8)
Insomnia | 126 (3.2) | 122 (3.1)
Myalgia | 114 (2.9) | 94 (2.4)
Angina pectoris | 101 (2.6) | 87 (2.2)
Rash | 96 (2.5) | 79 (2.0)
Pharyngitis | 91 (2.3) | 78 (2.0)
Asthenia | 90 (2.3) | 73 (1.9)
Pruritus | 87 (2.2) | 82 (2.1)
Flatulence | 84 (2.2) | 53 (1.4)
Spinal osteoarthritis | 82 (2.1) | 64 (1.7)
Gastroesophageal reflux disease | 80 (2.1) | 66 (1.7)
Herpes zoster | 79 (2.0) | 72 (1.9)

Hypocalcemia

Decreases in serum calcium levels to less than 8.5 mg/dL at any visit were reported in 0.4% women in the placebo group and 1.7% women in the denosumab group. The nadir in serum calcium level occurred at approximately day 10 after denosumab dosing in subjects with normal renal function.

In clinical studies, subjects with impaired renal function were more likely to have greater reductions in serum calcium levels compared to subjects with normal renal function. In a study of 55 subjects with varying degrees of renal function, serum calcium levels < 7.5 mg/dL or symptomatic hypocalcemia were observed in 5 subjects. These included no subjects in the normal renal function group, 10% of subjects in the creatinine clearance 50 to 80 mL/min group, 29% of subjects in the creatinine clearance < 30 mL/min group, and 29% of subjects in the hemodialysis group. These subjects did not receive calcium and vitamin D supplementation. In a study of 4550 postmenopausal women with osteoporosis, the mean change from baseline in serum calcium level 10 days after denosumab dosing was -5.5% in subjects with creatinine clearance < 30 mL/min vs. -3.1% in subjects with creatinine clearance ≥ 30 mL/min.

Serious Infections

Receptor activator of nuclear factor kappa-B ligand (RANKL) is expressed on activated T and B lymphocytes and in lymph nodes. Therefore, a RANKL inhibitor such as denosumab products may increase the risk of infection.

In the clinical study of 7808 postmenopausal women with osteoporosis, the incidence of infections resulting in death was 0.2% in both placebo and denosumab treatment groups. However, the incidence of nonfatal serious infections was 3.3% in the placebo and 4.0% in the denosumab groups. Hospitalizations due to serious infections in the abdomen (0.7% placebo vs. 0.9% denosumab), urinary tract (0.5% placebo vs. 0.7% denosumab), and ear (0.0% placebo vs. 0.1% denosumab) were reported. Endocarditis was reported in no placebo patients and 3 patients receiving denosumab.

Skin infections, including erysipelas and cellulitis, leading to hospitalization were reported more frequently in patients treated with denosumab (< 0.1% placebo vs. 0.4% denosumab).

The incidence of opportunistic infections was similar to that reported with placebo.

Dermatologic Adverse Reactions

A significantly higher number of patients treated with denosumab developed epidermal and dermal adverse events (such as dermatitis, eczema, and rashes), with these events reported in 8.2% of the placebo and 10.8% of the denosumab groups (p < 0.0001). Most of these events were not specific to the injection site [see Warnings and Precautions (5.8)].

Osteonecrosis of the Jaw

ONJ has been reported in the osteoporosis clinical trial program in patients treated with denosumab [see Warnings and Precautions (5.4)].

Atypical Subtrochanteric and Diaphyseal Femoral Fractures

In the osteoporosis clinical trial program, atypical femoral fractures were reported in patients treated with denosumab. The duration of denosumab exposure to time of atypical femoral fracture diagnosis was as early as 2½ years [see Warnings and Precautions (5.5)].

Multiple Vertebral Fractures (MVF) Following Treatment Discontinuation

In the osteoporosis clinical trial program, multiple vertebral fractures were reported in patients after discontinuation of denosumab. In the phase 3 trial in women with postmenopausal osteoporosis, 6% of women who discontinued denosumab and remained in the study developed new vertebral fractures, and 3% of women who discontinued denosumab and remained in the study developed multiple new vertebral fractures. The mean time to onset of multiple vertebral fractures was 17 months (range: 7-43 months) after the last injection of denosumab. Prior vertebral fracture was a predictor of multiple vertebral fractures after discontinuation [see Warnings and Precautions (5.6)].

Pancreatitis

Pancreatitis was reported in 4 patients (0.1%) in the placebo and 8 patients (0.2%) in the denosumab groups. Of these reports, 1 patient in the placebo group and all 8 patients in the denosumab group had serious events, including one death in the denosumab group. Several patients had a prior history of pancreatitis. The time from product administration to event occurrence was variable.

New Malignancies

The overall incidence of new malignancies was 4.3% in the placebo and 4.8% in the denosumab groups. New malignancies related to the breast (0.7% placebo vs. 0.9% denosumab), reproductive system (0.2% placebo vs. 0.5% denosumab), and gastrointestinal system (0.6% placebo vs. 0.9% denosumab) were reported. A causal relationship to drug exposure has not been established.

Treatment to Increase Bone Mass in Men with Osteoporosis

The safety of denosumab in the treatment of men with osteoporosis was assessed in a 1-year randomized, double-blind, placebo-controlled study. A total of 120 men were exposed to placebo and 120 men were exposed to denosumab administered subcutaneously once every 6 months as a single 60 mg dose. All men were instructed to take at least 1000 mg of calcium and 800 IU of vitamin D supplementation per day.

The incidence of all-cause mortality was 0.8% (n = 1) in the placebo group and 0.8% (n = 1) in the denosumab group. The incidence of nonfatal serious adverse events was 7.5% in the placebo group and 8.3% in the denosumab group. The percentage of patients who withdrew from the study due to adverse events was 0% and 2.5% for the placebo and denosumab groups, respectively.

Adverse reactions reported in ≥ 5% of men with osteoporosis and more frequently with denosumab than in the placebo-treated patients were: back pain (6.7% placebo vs. 8.3% denosumab), arthralgia (5.8% placebo vs. 6.7% denosumab), and nasopharyngitis (5.8% placebo vs. 6.7% denosumab).

Serious Infections

Serious infection was reported in 1 patient (0.8%) in the placebo group and no patients in the denosumab group.

Dermatologic Adverse Reactions

Epidermal and dermal adverse events (such as dermatitis, eczema, and rashes) were reported in 4 patients (3.3%) in the placebo group and 5 patients (4.2%) in the denosumab group.

Osteonecrosis of the Jaw

No cases of ONJ were reported.

Pancreatitis

Pancreatitis was reported in 1 patient (0.8%) in the placebo group and 1 patient (0.8%) in the denosumab group.

New Malignancies

New malignancies were reported in no patients in the placebo group and 4 (3.3%) patients (3 prostate cancers, 1 basal cell carcinoma) in the denosumab group.

Treatment of Glucocorticoid-Induced Osteoporosis

The safety of denosumab in the treatment of glucocorticoid-induced osteoporosis was assessed in the 1-year, primary analysis of a 2-year randomized, multicenter, double-blind, parallel-group, active-controlled study of 795 patients (30% men and 70% women) aged 20 to 94 (mean age of 63 years) treated with greater than or equal to 7.5 mg/day oral prednisone (or equivalent). A total of 384 patients were exposed to 5 mg oral daily bisphosphonate (active-control) and 394 patients were exposed to denosumab administered once every 6 months as a 60 mg subcutaneous dose. All patients were instructed to take at least 1000 mg of calcium and 800 IU of vitamin D supplementation per day.

The incidence of all-cause mortality was 0.5% (n = 2) in the active-control group and 1.5% (n = 6) in the denosumab group. The incidence of serious adverse events was 17% in the active-control group and 16% in the denosumab group. The percentage of patients who withdrew from the study due to adverse events was 3.6% and 3.8% for the active-control and denosumab groups, respectively.

Adverse reactions reported in ≥ 2% of patients with glucocorticoid-induced osteoporosis and more frequently with denosumab than in the active-control-treated patients are shown in the table below.

Table 2. Adverse Reactions Occurring in ≥ 2% of Patients with Glucocorticoid-induced Osteoporosis and More Frequently with Denosumab than in Active-Control-treated Patients
Preferred Term | Denosumab (N = 394) n (%) | Oral Daily Bisphosphonate (Active-Control) (N = 384) n (%)
Back pain | 18 (4.6) | 17 (4.4)
Hypertension | 15 (3.8) | 13 (3.4)
Bronchitis | 15 (3.8) | 11 (2.9)
Headache | 14 (3.6) | 7 (1.8)
Dyspepsia | 12 (3.0) | 10 (2.6)
Urinary tract infection | 12 (3.0) | 8 (2.1)
Abdominal pain upper | 12 (3.0) | 7 (1.8)
Upper respiratory tract infection | 11 (2.8) | 10 (2.6)
Constipation | 11 (2.8) | 6 (1.6)
Vomiting | 10 (2.5) | 6 (1.6)
Dizziness | 9 (2.3) | 8 (2.1)
Fall | 8 (2.0) | 7 (1.8)
Polymyalgia rheumatica [Events of worsening of underlying polymyalgia rheumatica.] | 8 (2.0) | 1 (0.3)

Osteonecrosis of the Jaw

No cases of ONJ were reported.

Atypical Subtrochanteric and Diaphyseal Femoral Fractures

Atypical femoral fractures were reported in 1 patient treated with denosumab. The duration of denosumab exposure to time of atypical femoral fracture diagnosis was at 8.0 months [see Warnings and Precautions (5.5)].

Serious Infections

Serious infection was reported in 15 patients (3.9%) in the active-control group and 17 patients (4.3%) in the denosumab group.

Dermatologic Adverse Reactions

Epidermal and dermal adverse events (such as dermatitis, eczema, and rashes) were reported in 16 patients (4.2%) in the active-control group and 15 patients (3.8%) in the denosumab group.

Treatment of Bone Loss in Patients Receiving Androgen Deprivation Therapy for Prostate Cancer or Adjuvant Aromatase Inhibitor Therapy for Breast Cancer

The safety of denosumab in the treatment of bone loss in men with nonmetastatic prostate cancer receiving androgen deprivation therapy (ADT) was assessed in a 3-year, randomized, double-blind, placebo-controlled, multinational study of 1468 men aged 48 to 97 years. A total of 725 men were exposed to placebo and 731 men were exposed to denosumab administered once every 6 months as a single 60 mg subcutaneous dose. All men were instructed to take at least 1000 mg of calcium and 400 IU of vitamin D supplementation per day.

The incidence of serious adverse events was 30.6% in the placebo group and 34.6% in the denosumab group. The percentage of patients who withdrew from the study due to adverse events was 6.1% and 7.0% for the placebo and denosumab groups, respectively.

The safety of denosumab in the treatment of bone loss in women with nonmetastatic breast cancer receiving aromatase inhibitor (AI) therapy was assessed in a 2-year, randomized, double-blind, placebo-controlled, multinational study of 252 postmenopausal women aged 35 to 84 years. A total of 120 women were exposed to placebo and 129 women were exposed to denosumab administered once every 6 months as a single 60 mg subcutaneous dose. All women were instructed to take at least 1000 mg of calcium and 400 IU of vitamin D supplementation per day.

The incidence of serious adverse events was 9.2% in the placebo group and 14.7% in the denosumab group. The percentage of patients who withdrew from the study due to adverse events was 4.2% and 0.8% for the placebo and denosumab groups, respectively.

Adverse reactions reported in ≥ 10% of denosumab-treated patients receiving ADT for prostate cancer or adjuvant AI therapy for breast cancer, and more frequently than in the placebo-treated patients were: arthralgia (13.0% placebo vs. 14.3% denosumab) and back pain (10.5% placebo vs. 11.5% denosumab). Pain in extremity (7.7% placebo vs. 9.9% denosumab) and musculoskeletal pain (3.8% placebo vs. 6.0% denosumab) have also been reported in clinical trials. Additionally, in denosumab-treated men with nonmetastatic prostate cancer receiving ADT, a greater incidence of cataracts was observed (1.2% placebo vs. 4.7% denosumab).

Hypocalcemia (serum calcium < 8.4 mg/dL) was reported only in denosumab-treated patients (2.4% vs. 0.0%) at the month 1 visit.

6.2 Postmarketing Experience

Because postmarketing reactions are reported voluntarily from a population of uncertain size, it is not always possible to reliably estimate their frequency or establish a causal relationship to drug exposure.

The following adverse reactions have been identified during post-approval use of denosumab products:

- Drug-related hypersensitivity reactions: anaphylaxis, rash, urticaria, facial swelling, and erythema
- Hypocalcemia: severe symptomatic hypocalcemia resulting in hospitalization, life-threatening events, and fatal cases
- Musculoskeletal pain, including severe cases
- Parathyroid hormone (PTH): Marked elevation in serum PTH in patients with severe renal impairment (creatinine clearance < 30 mL/min) or receiving dialysis
- Multiple vertebral fractures following treatment discontinuation
- Cutaneous and mucosal lichenoid drug eruptions (e.g. lichen planus-like reactions)
- Alopecia
- Vasculitis (e.g. ANCA positive vasculitis, leukocytoclastic vasculitis)
- Drug reaction with eosinophilia and systemic symptoms (DRESS) syndrome

8 USE IN SPECIFIC POPULATIONS

8.1 Pregnancy

Risk Summary

Ospomyv is contraindicated for use in pregnant women because it may cause harm to a fetus. There are insufficient data with denosumab products use in pregnant women to inform any drug-associated risks for adverse developmental outcomes. In utero denosumab exposure from cynomolgus monkeys dosed monthly with denosumab throughout pregnancy at a dose 50-fold higher than the recommended human dose based on body weight resulted in increased fetal loss, stillbirths, and postnatal mortality, and absent lymph nodes, abnormal bone growth, and decreased neonatal growth [see Data].

Data

Animal Data

The effects of denosumab on prenatal development have been studied in both cynomolgus monkeys and genetically engineered mice in which RANK ligand (RANKL) expression was turned off by gene removal (a "knockout mouse"). In cynomolgus monkeys dosed subcutaneously with denosumab throughout pregnancy starting at gestational day 20 and at a pharmacologically active dose 50-fold higher than the recommended human dose based on body weight, there was increased fetal loss during gestation, stillbirths, and postnatal mortality. Other findings in offspring included absence of axillary, inguinal, mandibular, and mesenteric lymph nodes; abnormal bone growth, reduced bone strength, reduced hematopoiesis, dental dysplasia, and tooth malalignment; and decreased neonatal growth. At birth out to 1 month of age, infants had measurable blood levels of denosumab (22-621% of maternal levels).

Following a recovery period from birth out to 6 months of age, the effects on bone quality and strength returned to normal; there were no adverse effects on tooth eruption, though dental dysplasia was still apparent; axillary and inguinal lymph nodes remained absent, while mandibular and mesenteric lymph nodes were present, though small; and minimal to moderate mineralization in multiple tissues was seen in one recovery animal. There was no evidence of maternal harm prior to labor; adverse maternal effects occurred infrequently during labor. Maternal mammary gland development was normal. There was no fetal NOAEL (no observable adverse effect level) established for this study because only one dose of 50 mg/kg was evaluated. Mammary gland histopathology at 6 months of age was normal in female offspring exposed to denosumab in utero; however, development and lactation have not been fully evaluated.

In RANKL knockout mice, absence of RANKL (the target of denosumab) also caused fetal lymph node agenesis and led to postnatal impairment of dentition and bone growth. Pregnant RANKL knockout mice showed altered maturation of the maternal mammary gland, leading to impaired lactation [see Use in Specific Populations (8.2), Nonclinical Toxicology (13.2)].

The no effect dose for denosumab product-induced teratogenicity is unknown. However, a Cmax of 22.9 ng/mL was identified in cynomolgus monkeys as a level in which no biologic effects (NOEL) of denosumab were observed (no inhibition of RANKL) [see Clinical Pharmacology (12.3)].

8.2 Lactation

Risk Summary

There is no information regarding the presence of denosumab products in human milk, the effects on the breastfed infant, or the effects on milk production. Denosumab was detected in the maternal milk of cynomolgus monkeys up to 1 month after the last dose of denosumab (≤ 0.5% milk:serum ratio) and maternal mammary gland development was normal, with no impaired lactation. However, pregnant RANKL knockout mice showed altered maturation of the maternal mammary gland, leading to impaired lactation [see Use in Specific Populations (8.1), Nonclinical Toxicology (13.2)].

8.3 Females and Males of Reproductive Potential

Based on findings in animals, denosumab products can cause fetal harm when administered to a pregnant woman [see Use in Specific Populations (8.1)].

Pregnancy Testing

Verify the pregnancy status of females of reproductive potential prior to initiating Ospomyv treatment.

Contraception

Females

Advise females of reproductive potential to use effective contraception during therapy, and for at least 5 months after the last dose of Ospomyv.

Males

Denosumab was present at low concentrations (approximately 2% of serum exposure) in the seminal fluid of male subjects given denosumab. Following vaginal intercourse, the maximum amount of denosumab delivered to a female partner would result in exposures approximately 11000 times lower than the prescribed 60 mg subcutaneous dose, and at least 38 times lower than the NOEL in monkeys.

Therefore, male condom use would not be necessary as it is unlikely that a female partner or fetus would be exposed to pharmacologically relevant concentrations of denosumab products via seminal fluid [see Clinical Pharmacology (12.3)].

8.4 Pediatric Use

The safety and effectiveness of Ospomyv have not been established in pediatric patients.

In one multicenter, open-label study with denosumab conducted in 153 pediatric patients with osteogenesis imperfecta, aged 2 to 17 years, evaluating fracture risk reduction, efficacy was not demonstrated.

Hypercalcemia has been reported in pediatric patients with osteogenesis imperfecta treated with denosumab products. Some cases required hospitalization and were complicated by acute renal injury [see Warnings and Precautions (5.11)]. Clinical studies in pediatric patients with osteogenesis imperfecta were terminated early due to the occurrence of life-threatening events and hospitalizations due to hypercalcemia.

Safety and effectiveness were not demonstrated for the treatment of glucocorticoid-induced osteoporosis in one multicenter, randomized, double-blind, placebo-controlled, parallel-group study conducted in 24 pediatric patients with glucocorticoid-induced osteoporosis, aged 5 to 17 years, evaluating change from baseline in lumbar spine BMD Z-score.

Based on results from animal studies, denosumab may negatively affect long-bone growth and dentition in pediatric patients below the age of 4 years.

Juvenile Animal Toxicity Data

Treatment with denosumab products may impair long-bone growth in children with open growth plates and may inhibit eruption of dentition. In neonatal rats, inhibition of RANKL (the target of denosumab therapy) with a construct of osteoprotegerin bound to Fc (OPG-Fc) at doses ≤ 10 mg/kg was associated with inhibition of bone growth and tooth eruption. Adolescent primates treated with denosumab at doses 10 and 50 times (10 and 50 mg/kg dose) higher than the recommended human dose of 60 mg administered every 6 months, based on body weight (mg/kg), had abnormal growth plates, considered to be consistent with the pharmacological activity of denosumab [see Nonclinical Toxicology (13.2)].

Cynomolgus monkeys exposed in utero to denosumab exhibited bone abnormalities, an absence of axillary, inguinal, mandibular, and mesenteric lymph nodes, reduced hematopoiesis, tooth malalignment, and decreased neonatal growth. Some bone abnormalities recovered once exposure was ceased following birth; however, axillary and inguinal lymph nodes remained absent 6 months post-birth [see Use in Specific Populations (8.1)].

8.5 Geriatric Use

Of the total number of patients in clinical studies of denosumab, 9943 patients (76%) were ≥ 65 years old, while 3576 (27%) were ≥ 75 years old. Of the patients in the osteoporosis study in men, 133 patients (55%) were ≥ 65 years old, while 39 patients (16%) were ≥ 75 years old. Of the patients in the glucocorticoid-induced osteoporosis study, 355 patients (47%) were ≥ 65 years old, while 132 patients (17%) were ≥ 75 years old. No overall differences in safety or efficacy were observed between these patients and younger patients, and other reported clinical experience has not identified differences in responses between the elderly and younger patients, but greater sensitivity of some older individuals cannot be ruled out.

8.6 Renal Impairment

No dose adjustment is necessary in patients with renal impairment.

Severe hypocalcemia resulting in hospitalization, life-threatening events and fatal cases have been reported postmarketing. In clinical studies, patients with advanced chronic kidney disease (i.e., eGFR < 30 mL/min/1.73 m^2), including dialysis-dependent patients, were at greater risk of developing hypocalcemia. The presence of underlying chronic kidney disease-mineral bone disorder (CKD-MBD, renal osteodystrophy) markedly increases the risk of hypocalcemia. Concomitant use of calcimimetic drugs may also worsen hypocalcemia risk. Consider the benefits and risks to the patient when administering Ospomyv to patients with advanced chronic kidney disease. Monitor calcium and mineral levels (phosphorus and magnesium). Adequate intake of calcium and vitamin D is important in patients with advanced chronic kidney disease including dialysis-dependent patients [see Dosage and Administration (2.2), Warnings and Precautions (5.1), Adverse Reactions (6.1) and Clinical Pharmacology (12.3)].

11 DESCRIPTION

Denosumab-dssb is a human IgG2 monoclonal antibody with affinity and specificity for human RANKL (receptor activator of nuclear factor kappa-B ligand). Denosumab-dssb has an approximate molecular weight of 147 kDa and is produced in genetically engineered mammalian (Chinese hamster ovary) cells.

Ospomyv (denosumab-dssb) injection is a sterile, preservative-free, clear, colorless to slightly yellow solution for subcutaneous use.

Each single-dose prefilled syringe contains1 mL solution of 60 mg denosumab-dssb, 0.28 mg histidine, 3.81 mg histidine hydrochloride monohydrate, 0.1 mg polysorbate 20, 44 mg sorbitol, and Water for Injections. The pH is 5.2.

12 CLINICAL PHARMACOLOGY

12.1 Mechanism of Action

Denosumab products bind to RANKL, a transmembrane or soluble protein essential for the formation, function, and survival of osteoclasts, the cells responsible for bone resorption. Denosumab products prevent RANKL from activating its receptor, RANK, on the surface of osteoclasts and their precursors. Prevention of the RANKL/RANK interaction inhibits osteoclast formation, function, and survival, thereby decreasing bone resorption and increasing bone mass and strength in both cortical and trabecular bone.

12.2 Pharmacodynamics

In clinical studies, treatment with 60 mg of denosumab resulted in reduction in the bone resorption marker serum type 1 C-telopeptide (CTX) by approximately 85% by 3 days, with maximal reductions occurring by 1 month. CTX levels were below the limit of assay quantitation (0.049 ng/mL) in 39% to 68% of patients 1 to 3 months after dosing of denosumab. At the end of each dosing interval, CTX reductions were partially attenuated from a maximal reduction of ≥ 87% to ≥ 45% (range: 45% to 80%), as serum denosumab levels diminished, reflecting the reversibility of the effects of denosumab on bone remodeling. These effects were sustained with continued treatment. Upon reinitiation, the degree of inhibition of CTX by denosumab was similar to that observed in patients initiating denosumab treatment.

Consistent with the physiological coupling of bone formation and resorption in skeletal remodeling, subsequent reductions in bone formation markers (i.e. osteocalcin and procollagen type 1 N-terminal peptide [P1NP]) were observed starting 1 month after the first dose of denosumab. After discontinuation of denosumab therapy, markers of bone resorption increased to levels 40% to 60% above pretreatment values but returned to baseline levels within 12 months.

12.3 Pharmacokinetics

In a study conducted in healthy male and female volunteers (n = 73, age range: 18 to 64 years) following a single subcutaneously administered denosumab dose of 60 mg, the mean area-under-the-concentration-time curve up to 16 weeks (AUC0-16 weeks) of denosumab was 316 mcg∙day/mL (standard deviation [SD] = 101 mcg∙day/mL). The mean maximum denosumab concentration (Cmax) was 6.75 mcg/mL (SD = 1.89 mcg/mL). No accumulation or change in denosumab pharmacokinetics with time is observed with multiple dosing of 60 mg subcutaneously administered once every 6 months.

Absorption

Following subcutaneous administration, the median time to maximum denosumab concentration (Tmax) was 10 days (range: 3 to 21 days).

Distribution

The mean volume of distribution for denosumab was 5.2 L (SD = 1.7 L).

Elimination

Serum denosumab concentrations declined over a period of 4 to 5 months with a mean half-life of 25.4 days (SD = 8.5 days; n = 46).

A population pharmacokinetic analysis was performed to evaluate the effects of demographic characteristics. This analysis showed no notable differences in pharmacokinetics with age (in postmenopausal women), race, or body weight (36 to 140 kg).

Seminal Fluid Pharmacokinetic Study

Serum and seminal fluid concentrations of denosumab were measured in 12 healthy male volunteers (age range: 43-65 years). After a single 60 mg subcutaneous administration of denosumab, the mean (± SD) Cmax values in the serum and seminal fluid samples were 6170 (± 2070) and 100 (± 81.9) ng/mL, respectively, resulting in a maximum seminal fluid concentration of approximately 2% of serum levels. The median (range) Tmax values in the serum and seminal fluid samples were 8.0 (7.9 to 21) and 21 (8.0 to 49) days, respectively. Among the subjects, the highest denosumab concentration in seminal fluid was 301 ng/mL at 22 days post-dose. On the first day of measurement (10 days post-dose), nine of eleven subjects had quantifiable concentrations in semen. On the last day of measurement (106 days post-dose), five subjects still had quantifiable concentrations of denosumab in seminal fluid, with a mean (± SD) seminal fluid concentration of 21.1 (± 36.5) ng/mL across all subjects (n = 12).

Drug Interactions

In a study of 19 postmenopausal women with low BMD and rheumatoid arthritis treated with etanercept (50 mg subcutaneous injection once weekly), a single-dose of denosumab (60 mg subcutaneous injection) was administered 7 days after the previous dose of etanercept. No clinically significant changes in the pharmacokinetics of etanercept were observed.

Cytochrome P450 substrates

In a study of 17 postmenopausal women with osteoporosis, midazolam (2 mg oral) was administered 2 weeks after a single-dose of denosumab (60 mg subcutaneous injection), which approximates the Tmax of denosumab. Denosumab did not affect the pharmacokinetics of midazolam, which is metabolized by cytochrome P450 3A4 (CYP3A4). This indicates that denosumab products should not alter the pharmacokinetics of drugs metabolized by CYP3A4 in postmenopausal women with osteoporosis.

Specific Populations

Gender: Mean serum denosumab concentration-time profiles observed in a study conducted in healthy men ≥ 50 years were similar to those observed in a study conducted in postmenopausal women using the same dose regimen.

Age: The pharmacokinetics of denosumab were not affected by age across all populations studied whose ages ranged from 28 to 87 years.

Race: The pharmacokinetics of denosumab were not affected by race.

Renal Impairment: In a study of 55 patients with varying degrees of renal function, including patients on dialysis, the degree of renal impairment had no effect on the pharmacokinetics of denosumab; thus, dose adjustment for renal impairment is not necessary.

Hepatic Impairment: No clinical studies have been conducted to evaluate the effect of hepatic impairment on the pharmacokinetics of denosumab products.

12.6 Immunogenicity

The observed incidence of anti-drug antibodies is highly dependent on the sensitivity and specificity of the assay. Differences in assay methods preclude meaningful comparisons of the incidence of anti-drug antibodies in the studies described below with the incidence of anti-drug antibodies in other studies, including those of denosumab or of other denosumab products.

Using an electrochemiluminescent bridging immunoassay, less than 1% (55 out of 8113) of patients treated with denosumab for up to 5 years tested positive for binding antibodies (including pre-existing, transient, and developing antibodies). None of the patients tested positive for neutralizing antibodies, as was assessed using a chemiluminescent cell-based in vitro biological assay.

There was no identified clinically significant effect of anti-drug antibodies on pharmacokinetics, pharmacodynamics, safety, or effectiveness of denosumab.

13 NONCLINICAL TOXICOLOGY

13.1 Carcinogenesis, Mutagenesis, Impairment of Fertility

Carcinogenicity

The carcinogenic potential of denosumab products has not been evaluated in long-term animal studies.

Mutagenicity

The genotoxic potential of denosumab products has not been evaluated.

Impairment of Fertility

Denosumab had no effect on female fertility or male reproductive organs in monkeys at doses that were 13- to 50-fold higher than the recommended human dose of 60 mg subcutaneously administered once every 6 months, based on body weight (mg/kg).

13.2 Animal Toxicology and/or Pharmacology

Denosumab products are inhibitors of osteoclastic bone resorption via inhibition of RANKL.

In ovariectomized monkeys, once-monthly treatment with denosumab suppressed bone turnover and increased BMD and strength of cancellous and cortical bone at doses 50-fold higher than the recommended human dose of 60 mg administered once every 6 months, based on body weight (mg/kg). Bone tissue was normal with no evidence of mineralization defects, accumulation of osteoid, or woven bone.

Because the biological activity of denosumab in animals is specific to nonhuman primates, evaluation of genetically engineered ("knockout") mice or use of other biological inhibitors of the RANK/RANKL pathway, namely OPG-Fc, provided additional information on the pharmacodynamic properties of denosumab products. RANK/RANKL knockout mice exhibited absence of lymph node formation, as well as an absence of lactation due to inhibition of mammary gland maturation (lobulo-alveolar gland development during pregnancy). Neonatal RANK/RANKL knockout mice exhibited reduced bone growth and lack of tooth eruption. A corroborative study in 2-week-old rats given the RANKL inhibitor OPG-Fc also showed reduced bone growth, altered growth plates, and impaired tooth eruption. These changes were partially reversible in this model when dosing with the RANKL inhibitors was discontinued.

14 CLINICAL STUDIES

14.1 Treatment of Postmenopausal Women with Osteoporosis

The efficacy and safety of denosumab in the treatment of postmenopausal osteoporosis was demonstrated in a 3-year, randomized, double-blind, placebo-controlled trial. Enrolled women had a baseline BMD T-score between -2.5 and -4.0 at either the lumbar spine or total hip. Women with other diseases (such as rheumatoid arthritis, osteogenesis imperfecta, and Paget's disease) or on therapies that affect bone were excluded from this study. The 7808 enrolled women were aged 60 to 91 years with a mean age of 72 years. Overall, the mean baseline lumbar spine BMD T-score was -2.8, and 23% of women had a vertebral fracture at baseline. Women were randomized to receive subcutaneous injections of either placebo (N = 3906) or denosumab 60 mg (N = 3902) once every 6 months. All women received at least 1000 mg calcium and 400 IU vitamin D supplementation daily.

The primary efficacy variable was the incidence of new morphometric (radiologically-diagnosed) vertebral fractures at 3 years. Vertebral fractures were diagnosed based on lateral spine radiographs (T4-L4) using a semiquantitative scoring method. Secondary efficacy variables included the incidence of hip fracture and nonvertebral fracture, assessed at 3 years.

Effect on Vertebral Fractures

Denosumab significantly reduced the incidence of new morphometric vertebral fractures at 1, 2, and 3 years (p < 0.0001), as shown in Table 3. The incidence of new vertebral fractures at year 3 was 7.2% in the placebo-treated women compared to 2.3% for the denosumab-treated women. The absolute risk reduction was 4.8% and relative risk reduction was 68% for new morphometric vertebral fractures at year 3.

Table 3. The Effect of Denosumab on the Incidence of New Vertebral Fractures in Postmenopausal Women
 | Proportion of Women with Fracture (%) [Event rates based on crude rates in each interval.] |  | Absolute Risk Reduction (%) [Absolute risk reduction and relative risk reduction based on Mantel-Haenszel method adjusting for age group variable.] (95% CI) | Relative Risk Reduction (%) (95% CI)
 | Placebo N = 3691 (%) | Denosumab N = 3702 (%) | Absolute Risk Reduction (%) [Absolute risk reduction and relative risk reduction based on Mantel-Haenszel method adjusting for age group variable.] (95% CI) | Relative Risk Reduction (%) (95% CI)
0-1 Year | 2.2 | 0.9 | 1.4 (0.8, 1.9) | 61 (42, 74)
0-2 Years | 5.0 | 1.4 | 3.5 (2.7, 4.3) | 71 (61, 79)
0-3 Years | 7.2 | 2.3 | 4.8 (3.9, 5.8) | 68 (59, 74)

Denosumab was effective in reducing the risk for new morphometric vertebral fractures regardless of age, baseline rate of bone turnover, baseline BMD, baseline history of fracture, or prior use of a drug for osteoporosis.

Effect on Hip Fractures

The incidence of hip fracture was 1.2% for placebo-treated women compared to 0.7% for denosumab-treated women at year 3. The age-adjusted absolute risk reduction of hip fractures was 0.3% with a relative risk reduction of 40% at 3 years (p = 0.04) (Figure 1).

Figure 1. Cumulative Incidence of Hip Fractures Over 3 Years

N = number of subjects randomized

Effect on Nonvertebral Fractures

Treatment with denosumab resulted in a significant reduction in the incidence of nonvertebral fractures (Table 4).

Table 4. The Effect of Denosumab on the Incidence of Nonvertebral Fractures at Year 3
 | Proportion of Women with Fracture (%) [Event rates based on Kaplan-Meier estimates at 3 years.] |  | Absolute Risk Reduction (%) (95% CI) | Relative Risk Reduction (%) (95% CI)
 | Placebo N = 3906 (%) | Denosumab N = 3902 (%) | Absolute Risk Reduction (%) (95% CI) | Relative Risk Reduction (%) (95% CI)
Nonvertebral fracture [Excluding those of the vertebrae (cervical, thoracic, and lumbar), skull, facial, mandible, metacarpus, and finger and toe phalanges.] | 8.0 | 6.5 | 1.5 (0.3, 2.7) | 20 (5, 33) [p-value = 0.01.]

Effect on Bone Mineral Density (BMD)

Treatment with denosumab significantly increased BMD at all anatomic sites measured at 3 years. The treatment differences in BMD at 3 years were 8.8% at the lumbar spine, 6.4% at the total hip, and 5.2% at the femoral neck. Consistent effects on BMD were observed at the lumbar spine, regardless of baseline age, race, weight/body mass index (BMI), baseline BMD, and level of bone turnover.

After denosumab discontinuation, BMD returned to approximately baseline levels within 12 months.

Bone Histology and Histomorphometry

A total of 115 transiliac crest bone biopsy specimens were obtained from 92 postmenopausal women with osteoporosis at either month 24 and/or month 36 (53 specimens in denosumab group, 62 specimens in placebo group). Of the biopsies obtained, 115 (100%) were adequate for qualitative histology and 7 (6%) were adequate for full quantitative histomorphometry assessment.

Qualitative histology assessments showed normal architecture and quality with no evidence of mineralization defects, woven bone, or marrow fibrosis in patients treated with denosumab.

The presence of double tetracycline labeling in a biopsy specimen provides an indication of active bone remodeling, while the absence of tetracycline label suggests suppressed bone formation. In patients treated with denosumab, 35% had no tetracycline label present at the month 24 biopsy and 38% had no tetracycline label present at the month 36 biopsy, while 100% of placebo-treated patients had double label present at both time points. When compared to placebo, treatment with denosumab resulted in virtually absent activation frequency and markedly reduced bone formation rates. However, the long-term consequences of this degree of suppression of bone remodeling are unknown.

14.2 Treatment to Increase Bone Mass in Men with Osteoporosis

The efficacy and safety of denosumab in the treatment to increase bone mass in men with osteoporosis was demonstrated in a 1-year, randomized, double-blind, placebo-controlled trial. Enrolled men had a baseline BMD T-score between -2.0 and -3.5 at the lumbar spine or femoral neck. Men with a BMD T-score between -1.0 and -3.5 at the lumbar spine or femoral neck were also enrolled if there was a history of prior fragility fracture. Men with other diseases (such as rheumatoid arthritis, osteogenesis imperfecta, and Paget's disease) or on therapies that may affect bone were excluded from this study. The 242 men enrolled in the study ranged in age from 31 to 84 years with a mean age of 65 years. Men were randomized to receive SC injections of either placebo (n = 121) or denosumab 60 mg (n = 121) once every 6 months. All men received at least 1000 mg calcium and at least 800 IU vitamin D supplementation daily.

Effect on Bone Mineral Density (BMD)

The primary efficacy variable was percent change in lumbar spine BMD from baseline to 1-year. Secondary efficacy variables included percent change in total hip, and femoral neck BMD from baseline to 1-year.

Treatment with denosumab significantly increased BMD at 1-year. The treatment differences in BMD at 1-year were 4.8% (+0.9% placebo, +5.7% denosumab; (95% CI: 4.0, 5.6); p < 0.0001) at the lumbar spine, 2.0% (+0.3% placebo, +2.4% denosumab) at the total hip, and 2.2% (0.0% placebo, +2.1% denosumab) at femoral neck. Consistent effects on BMD were observed at the lumbar spine regardless of baseline age, race, BMD, testosterone concentrations, and level of bone turnover.

Bone Histology and Histomorphometry

A total of 29 transiliac crest bone biopsy specimens were obtained from men with osteoporosis at 12 months (17 specimens in denosumab group, 12 specimens in placebo group). Of the biopsies obtained, 29 (100%) were adequate for qualitative histology and, in denosumab patients, 6 (35%) were adequate for full quantitative histomorphometry assessment. Qualitative histology assessments showed normal architecture and quality with no evidence of mineralization defects, woven bone, or marrow fibrosis in patients treated with denosumab. The presence of double tetracycline labeling in a biopsy specimen provides an indication of active bone remodeling, while the absence of tetracycline label suggests suppressed bone formation. In patients treated with denosumab, 6% had no tetracycline label present at the month 12 biopsy, while 100% of placebo-treated patients had double label present. When compared to placebo, treatment with denosumab resulted in markedly reduced bone formation rates. However, the long-term consequences of this degree of suppression of bone remodeling are unknown.

14.3 Treatment of Glucocorticoid-Induced Osteoporosis

The efficacy and safety of denosumab in the treatment of patients with glucocorticoid-induced osteoporosis was assessed in the 12-month primary analysis of a 2-year, randomized, multicenter, double-blind, parallel-group, active-controlled study (NCT 01575873) of 795 patients (70% women and 30% men) aged 20 to 94 years (mean age of 63 years) treated with greater than or equal to 7.5 mg/day oral prednisone (or equivalent) for < 3 months prior to study enrollment and planning to continue treatment for a total of at least 6 months (glucocorticoid-initiating subpopulation; n = 290) or ≥ 3 months prior to study enrollment and planning to continue treatment for a total of at least 6 months (glucocorticoid-continuing subpopulation, n = 505). Enrolled patients < 50 years of age were required to have a history of osteoporotic fracture. Enrolled patients ≥ 50 years of age who were in the glucocorticoid-continuing subpopulation were required to have a baseline BMD T-score of ≤ -2.0 at the lumbar spine, total hip, or femoral neck; or a BMD T-score ≤ -1.0 at the lumbar spine, total hip, or femoral neck and a history of osteoporotic fracture.

Patients were randomized (1:1) to receive either an oral daily bisphosphonate (active-control, risedronate 5 mg once daily) (n = 397) or denosumab 60 mg subcutaneously once every 6 months (n = 398) for one year. Randomization was stratified by gender within each subpopulation. Patients received at least 1000 mg calcium and 800 IU vitamin D supplementation daily.

Effect on Bone Mineral Density (BMD)

In the glucocorticoid-initiating subpopulation, denosumab significantly increased lumbar spine BMD compared to the active-control at one year (Active-control 0.8%, denosumab 3.8%) with a treatment difference of 2.9% (p < 0.001). In the glucocorticoid-continuing subpopulation, denosumab significantly increased lumbar spine BMD compared to active-control at one year (Active-control 2.3%, denosumab 4.4%) with a treatment difference of 2.2% (p < 0.001). Consistent effects on lumbar spine BMD were observed regardless of gender; race; geographic region; menopausal status; and baseline age, lumbar spine BMD T-score, and glucocorticoid dose within each subpopulation.

Bone Histology

Bone biopsy specimens were obtained from 17 patients (11 in the active-control treatment group and 6 in the denosumab treatment group) at Month 12. Of the biopsies obtained, 17 (100%) were adequate for qualitative histology. Qualitative assessments showed bone of normal architecture and quality without mineralization defects or bone marrow abnormality. The presence of double tetracycline labeling in a biopsy specimen provides an indication of active bone remodeling, while the absence of tetracycline label suggests suppressed bone formation. In patients treated with active-control, 100% of biopsies had tetracycline label. In patients treated with denosumab, 1 (33%) had tetracycline label and 2 (67%) had no tetracycline label present at the 12-month biopsy. Evaluation of full quantitative histomorphometry including bone remodeling rates was not possible in the glucocorticoid-induced osteoporosis population treated with denosumab. The long-term consequences of this degree of suppression of bone remodeling in glucocorticoid-treated patients is unknown.

14.4 Treatment of Bone Loss in Men with Prostate Cancer

The efficacy and safety of denosumab in the treatment of bone loss in men with nonmetastatic prostate cancer receiving androgen deprivation therapy (ADT) were demonstrated in a 3-year, randomized (1:1), double-blind, placebo-controlled, multinational study. Men less than 70 years of age had either a BMD T-score at the lumbar spine, total hip, or femoral neck between -1.0 and -4.0, or a history of an osteoporotic fracture. The mean baseline lumbar spine BMD T-score was -0.4, and 22% of men had a vertebral fracture at baseline. The 1468 men enrolled ranged in age from 48 to 97 years (median 76 years). Men were randomized to receive subcutaneous injections of either placebo (n = 734) or denosumab 60 mg (n = 734) once every 6 months for a total of 6 doses. Randomization was stratified by age (< 70 years vs. ≥ 70 years) and duration of ADT at trial entry (≤ 6 months vs. > 6 months). Seventy-nine percent of patients received ADT for more than 6 months at study entry. All men received at least 1000 mg calcium and 400 IU vitamin D supplementation daily.

Effect on Bone Mineral Density (BMD)

The primary efficacy variable was percent change in lumbar spine BMD from baseline to month 24. An additional key secondary efficacy variable was the incidence of new vertebral fracture through month 36 diagnosed based on x-ray evaluation by two independent radiologists. Lumbar spine BMD was higher at 2 years in denosumab-treated patients as compared to placebo-treated patients [-1.0% placebo, +5.6% denosumab; treatment difference 6.7% (95% CI: 6.2, 7.1); p < 0.0001].

With approximately 62% of patients followed for 3 years, treatment differences in BMD at 3 years were 7.9% (-1.2% placebo, +6.8% denosumab) at the lumbar spine, 5.7% (-2.6% placebo, +3.2% denosumab) at the total hip, and 4.9% (-1.8% placebo, +3.0% denosumab) at the femoral neck. Consistent effects on BMD were observed at the lumbar spine in relevant subgroups defined by baseline age, BMD, and baseline history of vertebral fracture.

Effect on Vertebral Fractures

Denosumab significantly reduced the incidence of new vertebral fractures at 3 years (p = 0.0125), as shown in Table 5.

Table 5. The Effect of Denosumab on the Incidence of New Vertebral Fractures in Men with Nonmetastatic Prostate Cancer
 | Proportion of Men with Fracture (%) [Event rates based on crude rates in each interval.] |  | Absolute Risk Reduction (%) [Absolute risk reduction and relative risk reduction based on Mantel-Haenszel method adjusting for age group and ADT duration variables.] (95% CI) | Relative Risk Reduction (%) (95% CI)
 | Placebo N = 673 (%) | Denosumab N = 679 (%) | Absolute Risk Reduction (%) [Absolute risk reduction and relative risk reduction based on Mantel-Haenszel method adjusting for age group and ADT duration variables.] (95% CI) | Relative Risk Reduction (%) (95% CI)
0-1 Year | 1.9 | 0.3 | 1.6 (0.5, 2.8) | 85 (33, 97)
0-2 Years | 3.3 | 1.0 | 2.2 (0.7, 3.8) | 69 (27, 86)
0-3 Years | 3.9 | 1.5 | 2.4 (0.7, 4.1) | 62 (22, 81)

14.5 Treatment of Bone Loss in Women with Breast Cancer

The efficacy and safety of denosumab in the treatment of bone loss in women receiving adjuvant aromatase inhibitor (AI) therapy for breast cancer was assessed in a 2-year, randomized (1:1), double-blind, placebo-controlled, multinational study. Women had baseline BMD T-scores between -1.0 to -2.5 at the lumbar spine, total hip, or femoral neck, and had not experienced fracture after age 25. The mean baseline lumbar spine BMD T-score was -1.1, and 2.0% of women had a vertebral fracture at baseline. The 252 women enrolled ranged in age from 35 to 84 years (median 59 years). Women were randomized to receive subcutaneous injections of either placebo (n = 125) or denosumab 60 mg (n = 127) once every 6 months for a total of 4 doses. Randomization was stratified by duration of adjuvant AI therapy at trial entry (≤ 6 months vs. > 6 months). Sixty-two percent of patients received adjuvant AI therapy for more than 6 months at study entry. All women received at least 1000 mg calcium and 400 IU vitamin D supplementation daily.

Effect on Bone Mineral Density (BMD)

The primary efficacy variable was percent change in lumbar spine BMD from baseline to month 12. Lumbar spine BMD was higher at 12 months in denosumab-treated patients as compared to placebo-treated patients [-0.7% placebo, +4.8% denosumab; treatment difference 5.5% (95% CI: 4.8, 6.3); p < 0.0001].

With approximately 81% of patients followed for 2 years, treatment differences in BMD at 2 years were 7.6% (-1.4% placebo, +6.2% denosumab) at the lumbar spine, 4.7% (-1.0% placebo, +3.8% denosumab) at the total hip, and 3.6% (-0.8% placebo, +2.8% denosumab) at the femoral neck.

16 HOW SUPPLIED/STORAGE AND HANDLING

How Supplied

Ospomyv injection is a clear, colorless to slightly yellow solution supplied in a single-dose prefilled syringe with a safety guard.

60 mg/mL in a single-dose prefilled syringe | 1 per carton | NDC 83457-012-10

Storage and Handling

Store Ospomyv refrigerated at 2°C to 8°C (36°F to 46°F) in the original carton to protect from light. Do not freeze. Prior to administration, Ospomyv may be allowed to reach room temperature up to 25°C (77°F) in the original container. Once removed from the refrigerator, Ospomyv may be stored at room temperature for a single period of up to 60 days, but not exceeding the original expiry date. If not used within this period of up to 60 days, Ospomyv may be returned to the refrigerator for 28 days for future use. Do not use Ospomyv after the expiry date printed on the label.

Protect Ospomyv from direct light and heat.

Avoid vigorous shaking of Ospomyv.

17 PATIENT COUNSELING INFORMATION

Advise the patient to read the FDA-approved patient labeling (Medication Guide).

Hypocalcemia

Advise the patient to adequately supplement with calcium and vitamin D and instruct them on the importance of maintaining serum calcium levels while receiving Ospomyv [see Warnings and Precautions (5.1), Use in Specific Populations (8.6)]. Advise patients to seek prompt medical attention if they develop signs or symptoms of hypocalcemia.

Severe Hypocalcemia in Patients with Advanced Chronic Kidney Disease

Advise patients with advanced chronic kidney disease, including those who are dialysis-dependent, about the symptoms of hypocalcemia and the importance of maintaining serum calcium levels with adequate calcium and activated vitamin D supplementation. Advise these patients to have their serum calcium measured weekly for the first month after Ospomyv administration and monthly thereafter [see Dosage and Administration (2.2), Warnings and Precautions (5.1), Use in Specific Populations (8.6)].

Drug Products with Same Active Ingredient

Advise patients that if they receive Ospomyv, they should not receive other denosumab products concomitantly [see Warnings and Precautions (5.2)].

Hypersensitivity

Advise patients to seek prompt medical attention if signs or symptoms of hypersensitivity reactions occur. Advise patients who have had signs or symptoms of systemic hypersensitivity reactions that they should not receive denosumab products [see Warnings and Precautions (5.3), Contraindications (4)].

Osteonecrosis of the Jaw

Advise patients to maintain good oral hygiene during treatment with Ospomyv and to inform their dentist prior to dental procedures that they are receiving Ospomyv. Patients should inform their physician or dentist if they experience persistent pain and/or slow healing of the mouth or jaw after dental surgery [see Warnings and Precautions (5.4)].

Atypical Subtrochanteric and Diaphyseal Femoral Fractures

Advise patients to report new or unusual thigh, hip, or groin pain [see Warnings and Precautions (5.5)].

Multiple Vertebral Fractures (MVF) Following Treatment Discontinuation

Advise patients not to interrupt Ospomyv therapy without talking to their physician [see Warnings and Precautions (5.6)].

Serious Infections

Advise patients to seek prompt medical attention if they develop signs or symptoms of infections, including cellulitis [see Warnings and Precautions (5.7)].

Dermatologic Adverse Reactions

Advise patients to seek prompt medical attention if they develop signs or symptoms of dermatological reactions (such as dermatitis, rashes, and eczema) [see Warnings and Precautions (5.8)].

Musculoskeletal Pain

Inform patients that severe bone, joint, and/or muscle pain have been reported in patients taking denosumab products. Patients should report severe symptoms if they develop [see Warnings and Precautions (5.9)].

Pregnancy/Nursing

Counsel females of reproductive potential to use effective contraceptive measure to prevent pregnancy during treatment and for at least 5 months after the last dose of Ospomyv. Advise the patient to contact their physician immediately if pregnancy does occur during these times. Advise patients not to take Ospomyv while pregnant or breastfeeding. If a patient wishes to start breastfeeding after treatment, advise her to discuss the appropriate timing with her physician [see Contraindications (4), Use in Specific Populations (8.1)].

Schedule of Administration

Advise patients that if a dose of Ospomyv is missed, the injection should be administered as soon as convenient. Thereafter, schedule injections every 6 months from the date of the last injection.

Ospomyv™ (denosumab-dssb)

Manufactured by:
Samsung Bioepis Co., Ltd.,
76, Songdogyoyuk-ro, Yeonsu-gu,
Incheon, 21987, Republic of Korea

US License Number 2046

Manufactured for:
Cordavis Limited
Dublin, Ireland

MEDICATION GUIDE
Ospomyv™ (Os'-poe-miv)
(denosumab-dssb)
injection, for subcutaneous use

What is the most important information I should know about Ospomyv?
If you receive Ospomyv, you should not receive other denosumab products at the same time.
Ospomyv can cause serious side effects including:

- Increased risk of severe low calcium levels in your blood (hypocalcemia). Ospomyv may lower the calcium levels in your blood. If you have low blood calcium before you start receiving Ospomyv, it may get worse during treatment. Your low blood calcium must be treated before you receive Ospomyv. Talk to your doctor before starting Ospomyv. Your doctor may prescribe calcium and vitamin D to help prevent low calcium levels in your blood while you take Ospomyv. Take calcium and vitamin D as your doctor tells you to.
  If you have advanced chronic kidney disease (may or may not be on kidney dialysis), Ospomyv may increase your risk for severe low calcium levels in your blood, which could result in hospitalization, life-threatening events and death. A mineral and bone disorder associated with kidney disease called chronic kidney disease-mineral bone disorder (CKD-MBD) may increase your risk for severe low calcium levels in blood. Before you start Ospomyv and during treatment, your doctor may need to do certain blood tests to check for CKD-MBD.
  Most people with low blood calcium levels do not have symptoms, but some people may have symptoms. Call your doctor right away if you have symptoms of low blood calcium such as:

- spasms, twitches, or cramps in your muscles
- numbness or tingling in your fingers, toes, or around your mouth

- Serious allergic reactions. Serious allergic reactions have happened in people who take denosumab products. Call your doctor or go to your nearest emergency room right away if you have any symptoms of a serious allergic reaction. Symptoms of a serious allergic reaction may include:

- low blood pressure (hypotension)
- trouble breathing
- throat tightness
- swelling of your face, lips, or tongue

- rash
- itching
- hives

- Severe jaw bone problems (osteonecrosis). Severe jaw bone problems may happen when you take Ospomyv. Your doctor should examine your mouth before you start Ospomyv. Your doctor may tell you to see your dentist before you start Ospomyv. It is important for you to practice good mouth care during treatment with Ospomyv. Ask your doctor or dentist about good mouth care if you have any questions.
- Unusual thigh bone fractures. Some people have developed unusual fractures in their thigh bone. Symptoms of a fracture include new or unusual pain in your hip, groin, or thigh.
- Increased risk of broken bones, including broken bones in the spine, after stopping, skipping or delaying Ospomyv. Talk with your doctor before starting Ospomyv treatment. After your treatment with Ospomyv is stopped, or if you skip or delay taking a dose, your risk for breaking bones, including bones in your spine, is increased. Your risk for having more than 1 broken bone in your spine is increased if you have already had a broken bone in your spine. Do not stop, skip or delay taking Ospomyv without first talking with your doctor. If your Ospomyv treatment is stopped, talk to your doctor about other medicine that you can take.
- Serious infections. Serious infections in your skin, lower stomach area (abdomen), bladder, or ear may happen if you take Ospomyv. Inflammation of the inner lining of the heart (endocarditis) due to an infection also may happen more often in people who take Ospomyv. You may need to go to the hospital for treatment if you develop an infection.
  Ospomyv is a medicine that may affect the ability of your body to fight infections. People who have a weakened immune system or take medicines that affect the immune system may have an increased risk for developing serious infections. Call your doctor right away if you have any of the following symptoms of infection:

- fever or chills
- skin that looks red or swollen and is hot or tender to touch
- fever, shortness of breath, cough that will not go away
- severe abdominal pain
- frequent or urgent need to urinate or burning feeling when you urinate

- Skin problems. Skin problems such as inflammation of your skin (dermatitis), rash, and eczema may happen if you take Ospomyv. Call your doctor if you have any of the following symptoms of skin problems that do not go away or get worse:

- redness
- itching
- small bumps or patches (rash)

- your skin is dry or feels like leather
- blisters that ooze or become crusty
- skin peeling

- Bone, joint, or muscle pain. Some people who take denosumab products develop severe bone, joint, or muscle pain.

Call your doctor right away if you have any of these side effects.

What is Ospomyv?
Ospomyv is a prescription medicine used to:

- Treat osteoporosis (thinning and weakening of bone) in women after menopause ("change of life") who:
  - are at high risk for fracture (broken bone)
  - cannot use another osteoporosis medicine or other osteoporosis medicines did not work well
- Increase bone mass in men with osteoporosis who are at high risk for fracture.
- Treat osteoporosis in men and women who will be taking corticosteroid medicines (such as prednisone) for at least 6 months and are at high risk for fracture.
- Treat bone loss in men who are at high risk for fracture receiving certain treatments for prostate cancer that has not spread to other parts of the body.
- Treat bone loss in women who are at high risk for fracture receiving certain treatments for breast cancer that has not spread to other parts of the body.

It is not known if Ospomyv is safe and effective in children. Ospomyv is not approved for use in children.

Do not take Ospomyv if you:

- have been told by your doctor that your blood calcium level is too low.
- are pregnant or plan to become pregnant.
- are allergic to denosumab products or any of the ingredients in Ospomyv. See the end of this
  Medication Guide for a complete list of ingredients in Ospomyv.

Before taking Ospomyv, tell your doctor about all of your medical conditions, including if you:

- are taking other denosumab products.
- have low blood calcium.
- cannot take daily calcium and vitamin D.
- had parathyroid or thyroid surgery (glands located in your neck).
- have been told you have trouble absorbing minerals in your stomach or intestines (malabsorption syndrome).
- have kidney problems or are on kidney dialysis.
- are taking medicine that can lower your blood calcium levels.
- plan to have dental surgery or teeth removed.
- are pregnant or plan to become pregnant. Ospomyv may harm your unborn baby.
  Females who are able to become pregnant:
  - Your healthcare provider should do a pregnancy test before you start treatment with Ospomyv.
  - You should use an effective method of birth control (contraception) during treatment with Ospomyv and for at least 5 months after your last dose of Ospomyv.
  - Tell your doctor right away if you become pregnant while taking Ospomyv.
- are breastfeeding or plan to breastfeed. It is not known if Ospomyv passes into your breast milk. You and your doctor should decide if you will take Ospomyv or breastfeed. You should not do both.

Tell your doctor about all the medicines you take, including prescription and over-the-counter medicines, vitamins, and herbal supplements.
Know the medicines you take. Keep a list of medicines with you to show to your doctor or pharmacist when you get a new medicine.

How will I receive Ospomyv?

- Ospomyv is an injection that will be given to you by a healthcare provider. Ospomyv is injected under your skin (subcutaneous).
- You will receive Ospomyv 1 time every 6 months.
- You should take calcium and vitamin D as your doctor tells you to while you receive Ospomyv.
- If you miss a dose of Ospomyv, you should receive your injection as soon as you can.
- Take good care of your teeth and gums while you receive Ospomyv. Brush and floss your teeth regularly.

Tell your dentist that you are receiving Ospomyv before you have dental work.

What are the possible side effects of Ospomyv?
Ospomyv may cause serious side effects.

- See "What is the most important information I should know about Ospomyv?"
- It is not known if the use of Ospomyv over a long period of time may cause slow healing of broken bones.

The most common side effects of Ospomyv in women who are being treated for osteoporosis after menopause are:

- back pain
- pain in your arms and legs
- high cholesterol

- muscle pain
- bladder infection

The most common side effects of Ospomyv in men with osteoporosis are:

- back pain
- joint pain

- common cold (runny nose or sore throat)

The most common side effects of Ospomyv in patients with glucocorticoid-induced osteoporosis are:

- back pain
- high blood pressure

- lung infection (bronchitis)
- headache

The most common side effects of Ospomyv in patients receiving certain treatments for prostate or breast cancer are:

- back pain
- joint pain

- pain in your arms and legs
- muscle pain

Tell your doctor if you have any side effect that bothers you or that does not go away. These are not all the possible side effects of Ospomyv.
Call your doctor for medical advice about side effects. You may report side effects to FDA at 1-800-FDA-1088.

How should I store Ospomyv if I need to pick it up from a pharmacy?

- Keep Ospomyv refrigerated at 36°F to 46°F (2°C to 8°C) in the original carton.
- Do not freeze Ospomyv.
- When you remove Ospomyv from the refrigerator, Ospomyv must be kept at room temperature up to 77°F (25°C) in the original carton and must be used within 60 days. At the end of this period of up to 60 days, the product may be returned to the refrigerator for 28 days for future use. Do not use Ospomyv after the expiry date printed on the label.
- Do not keep Ospomyv at temperatures above 77°F (25°C). Warm temperatures will affect how Ospomyv works.
- Do not shake Ospomyv.
- Keep Ospomyv in the original carton to protect from light.

Keep Ospomyv and all medicines out of the reach of children.

General information about the safe and effective use of Ospomyv.
Medicines are sometimes prescribed for purposes other than those listed in a Medication Guide. Do not use Ospomyv for a condition for which it was not prescribed. Do not give Ospomyv to other people, even if they have the same symptoms that you have. It may harm them. You can ask your doctor or pharmacist for information about Ospomyv that is written for healthcare providers.

What are the ingredients in Ospomyv?
Active ingredient: denosumab-dssb
Inactive ingredients: histidine, histidine hydrochloride monohydrate, polysorbate 20, sorbitol, and water for injections
Manufactured by: Samsung Bioepis Co., Ltd., 76, Songdogyoyuk-ro, Yeonsu-gu, Incheon, 21987, Republic of Korea US License Number 2046
Manufactured for: Cordavis Limited, Dublin, Ireland
For more information, call at 1-833-267-3130.

This Medication Guide has been approved by the U.S. Food and Drug Administration.
Revised: 10/2025

PRINCIPAL DISPLAY PANEL - 60 mg/mL Syringe Carton

NDC 83457-012-10

OSPOMYV™
(denosumab-dssb)

60 mg/mL

Injection
For subcutaneous use only

1 x 60 mg/mL Single-dose Prefilled Syringe

Rx only
cordavis™

Single-dose Prefilled Syringe. Discard unused portion.
Sterile Solution – No preservative.

Ospomyv should be administered by a healthcare
provider

ATTENTION: Dispense the accompanying
Medication Guide to each patient.
For more copies call 1-833-267-3130.

OPEN
⯆